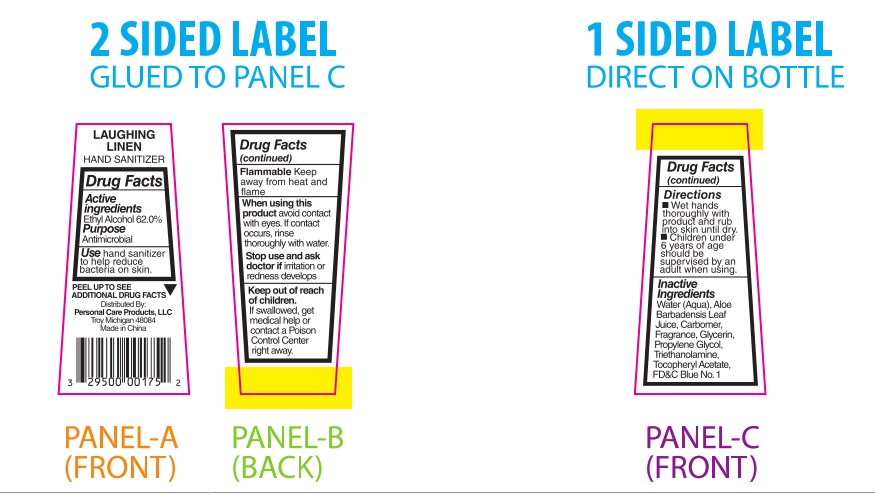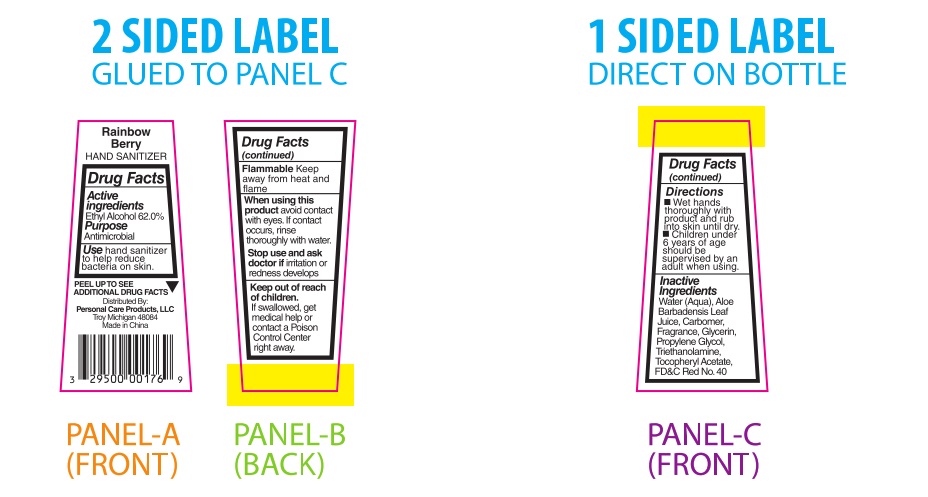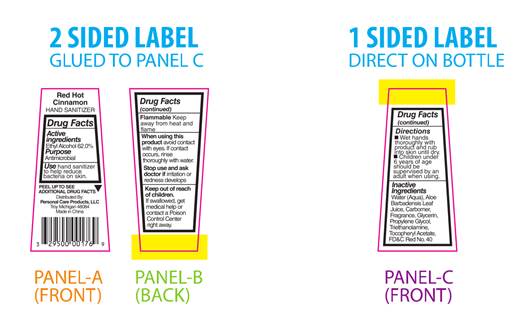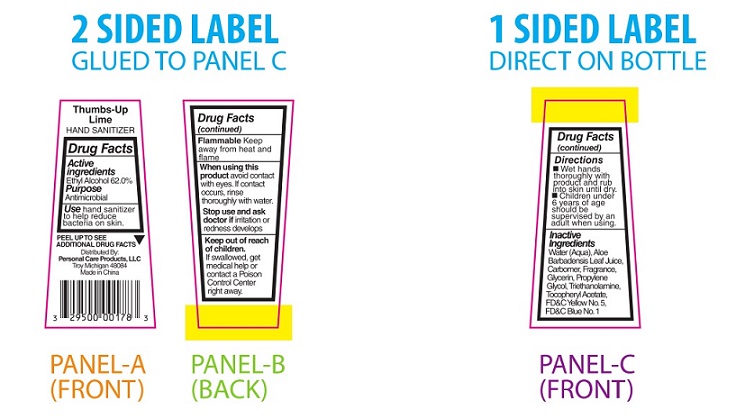 DRUG LABEL: Laughing Linen
NDC: 29500-9815 | Form: LIQUID
Manufacturer: GL360
Category: otc | Type: HUMAN OTC DRUG LABEL
Date: 20180610

ACTIVE INGREDIENTS: ALCOHOL 17.57 g/30 mL
INACTIVE INGREDIENTS: water; ALOE VERA LEAF; CARBOXYPOLYMETHYLENE; GLYCERIN; PROPYLENE GLYCOL; TROLAMINE; .ALPHA.-TOCOPHEROL ACETATE; FD&C BLUE NO. 1

Laughing Linen - 9815
Rainbow Berry - 9816
Red Hot Cinnamon -9817
Thumbs-Up Lime - 9818

DRUG FACTS

Active Ingredients

Ethyl Alcohol 62.0%

Purpose

Antimicrobial

INDICATIONS AND USAGE

Use hand sanitizer
to help reduce
bacteria on skin.

WARNINGS

Flammable

Keep away from heat and
flame.

When using this
product avoid contact
with eyes. If contact
occurs, rinse
thoroughly with water.

Stop use and ask
doctor if irritation or
redness develops

Keep out of reach of children.
If swallowed, get medical help or
contact a PoisonControl Center
right away.

Directions
■ Wet hands thoroughly with
product and rub into skin until dry.
■ Children under 6 years of age
should be supervised by an adult when using.

Inactive
Ingredients
Water (Aqua), Aloe
Barbadensis Leaf Juice,
Carbomer, Fragrance,
Glycerin, Propylene
Glycol, Triethanolamine,
Tocopheryl Acetate, FD&C Blue No. 1

PACKAGE LABEL

Laughing Linen

HAND SANITIZER

Drug Facts

Active
Ingredients
Ethyl Alcohol 62.0%

Purpose
Antimicrobial

Use hand sanitizer
to help reduce
bacteria on skin.

PEEL TO SEE ▼
ADDITIONAL DRUG FACTS

Distributed By:
Personal Care Products, LLC
Troy, Michigan 48084
Made in China

Drug Facts
(continued)

Flammable Keep
away from heat and
flame

When using this
product avoid contact
with eyes. If contact
occurs, rinse
thoroughly with water.

Stop use and ask
doctor if irritation or
redness develops

Keep out of reach
of children.
If swallowed, get
medical help or
contact a Poison
Control Center
right away.

Drug Facts
(continued)

Directions
■ Wet hands
thoroughly with
product and rub
into skin until dry.
■ Children under
6 years of age
should be
supervised by an
adult when using.

Inactive
IngredientsWater (Aqua), Aloe
Barbadensis Leaf Juice,
Carbomer, Fragrance,
Glycerin, Propylene
Glycol, Triethanolamine,
Tocopheryl Acetate,
FD&C Blue No. 1

___________________________________________________________________________________________________________________

PACKAGE LABEL

Rainbow Berry

Rainbow Berry
HAND SANITIZER

Drug Facts

Active
Ingredients
Ethyl Alcohol 62.0%

Purpose
Antimicrobial

Usehand sanitizer
to help reduce
bacteria on skin.

PEEL TO SEE ▼
ADDITIONAL DRUG FACTS

Distributed By:
Personal Care Products, LLC
Troy, Michigan 48084
Made in China

Drug Facts
(continued)

Flammable Keep
away from heat and
flame

When using this
product avoid contact
with eyes. If contact
occurs, rinse
thoroughly with water.

Stop use and ask
doctor if irritation or
redness develops

Keep out of reach
of children.
If swallowed, get
medical help or
contact a Poison
Control Center
right away.

Drug Facts
(continued)

Directions
■ Wet hands
thoroughly with
product and rub
into skin until dry.
■ Children under
6 years of age
should be
supervised by an
adult when using.

Inactive
IngredientsWater (Aqua), Aloe
Barbadensis Leaf Juice,
Carbomer, Fragrance,
Glycerin, Propylene
Glycol, Triethanolamine,
Tocopheryl Acetate, FD&C Red No. 40

PACKAGE LABEL

Red Hot Cinnamon
HAND SANITIZER

Drug Facts

Active
Ingredients
Ethyl Alcohol 62.0%

Purpose
Antimicrobial

Use hand sanitizer
to help reduce
bacteria on skin.

PEEL TO SEE ▼
ADDITIONAL DRUG FACTS

Distributed By:
Personal Care Products, LLC
Troy, Michigan 48084
Made in China

Drug Facts
(continued)

Flammable Keep
away from heat and
flame

When using this
product avoid contact
with eyes. If contact
occurs, rinse
thoroughly with water.

Stop use and ask
doctor if irritation or
redness develops

Keep out of reach
of children.
If swallowed, get
medical help or
contact a Poison
Control Center
right away.

Drug Facts
(continued)

Directions
■ Wet hands
thoroughly with
product and rub
into skin until dry.
■ Children under
6 years of age
should be
supervised by an
adult when using.

Inactive
Ingredients
Water (Aqua), Aloe
Barbadensis Leaf Juice,
Carbomer, Fragrance,
Glycerin, Propylene
Glycol, Triethanolamine,
Tocopheryl Acetate,
FD&C Red No. 40

PACKAGE LABEL

Thumbs-Up Lime
HAND SANITIZER

Drug Facts

Active
Ingredients
Ethyl Alcohol 62.0%

Purpose
Antimicrobial

Use hand sanitizer
to help reduce
bacteria on skin.

PEEL TO SEE ▼
ADDITIONAL DRUG FACTS

Distributed By:
Personal Care Products, LLC
Troy, Michigan 48084
Made in China

Drug Facts
(continued)

Flammable Keep
away from heat and
flame

When using this
product avoid contact
with eyes. If contact
occurs, rinse
thoroughly with water.

Stop use and ask
doctor if irritation or
redness develops

Keep out of reach
of children.
If swallowed, get
medical help or
contact a Poison
Control Center
right away.

Drug Facts
(continued)

Directions
■ Wet hands
thoroughly with
product and rub
into skin until dry.
■ Children under
6 years of age
should be
supervised by an
adult when using.

Inactive
Ingredients
Water (Aqua), Aloe
Barbadensis Leaf Juice,
Carbomer, Fragrance,
Glycerin, Propylene
Glycol, Triethanolamine,
Tocopheryl Acetate,
FD&C Yellow No. 5,
FD&C Blue No.1